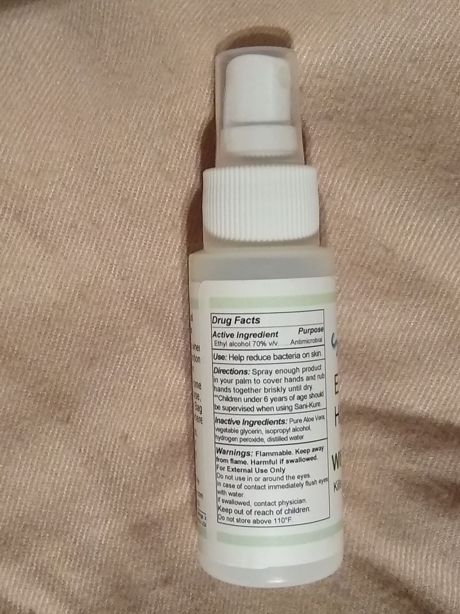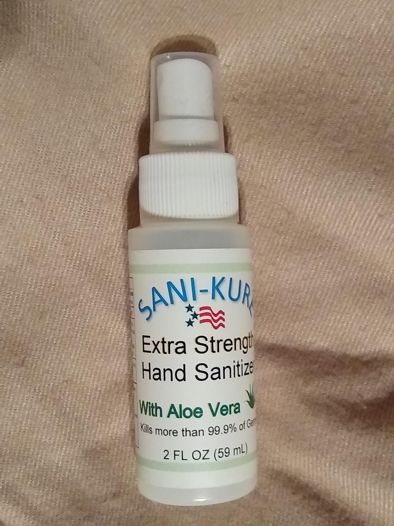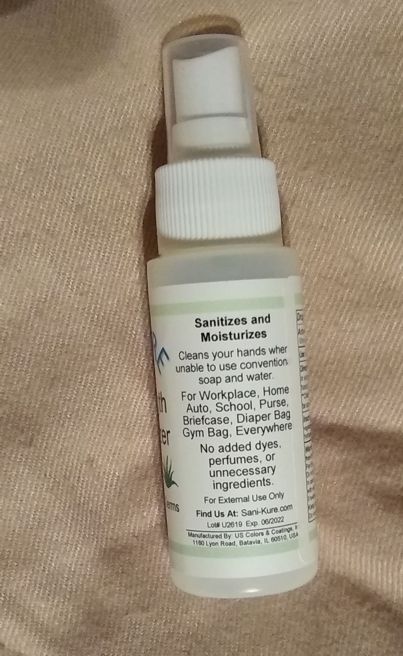 DRUG LABEL: Sani-Kure Extra Strength Hand Sanitizer
NDC: 78923-001 | Form: SOLUTION
Manufacturer: KOLORCURE CORPORATION
Category: otc | Type: HUMAN OTC DRUG LABEL
Date: 20220119

ACTIVE INGREDIENTS: ALCOHOL 74 mL/100 mL
INACTIVE INGREDIENTS: GLYCERIN 2.1 mL/100 mL; HYDROGEN PEROXIDE 1.8 mL/100 mL; WATER 7.1 mL/100 mL; ALOE VERA WHOLE 15 mL/100 mL

Active Ingredient(s)

Alcohol 70% v/v. Purpose: Antimicrobial

Use:

Antimicrobial

Warnings

Flammable. Keep away from heat or flame. Harmful if swallowed. For external use only.

Do not use

in or around the eys.

WHEN USING

In case of contact immediately flush eyes with water.
If swallowed, contact physician.
Keep out of reach of children.

Directions

- Place enough product in your palm to cover hands. Rub hands together until dry.
- Children under 6 years of age should be supervised when using Sani-Kure.

Other information

Do not store above 110°F.

Inactive ingredients

Pure Aloe Vera, vegetable glycerin, isopropyl alcohol, hydrogen peroxide, distilled water.

Warnings

Keep out of reach of children.

Package Label - Principal Display Panel

2 FL OZ (59 mL)